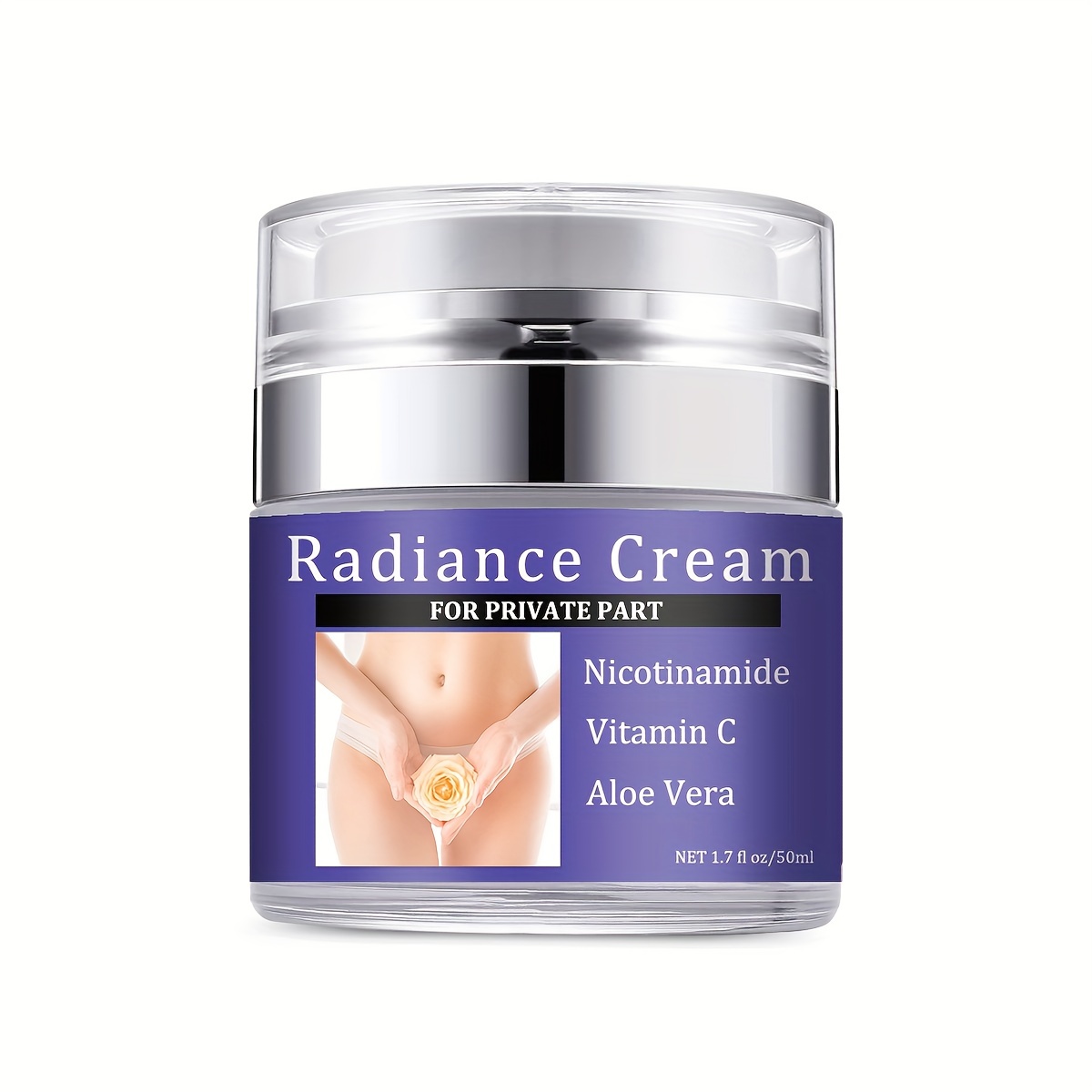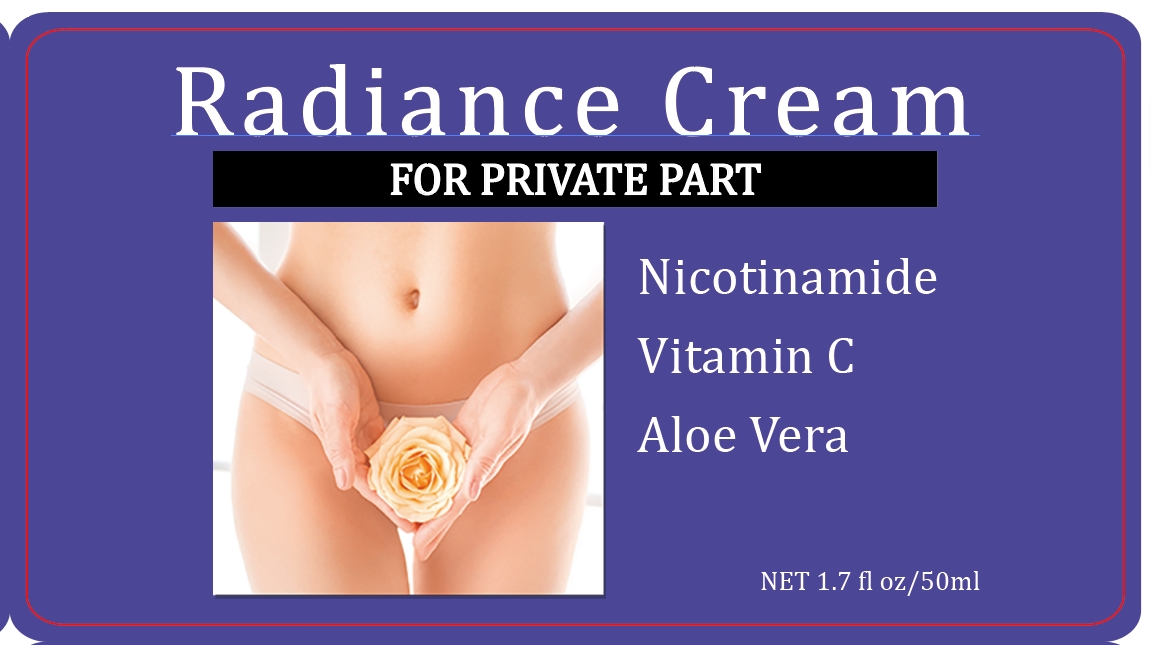 DRUG LABEL: Radiance Cream
NDC: 84025-031 | Form: CREAM
Manufacturer: Guangzhou Yanxi Biotechnology Co., Ltd
Category: otc | Type: HUMAN OTC DRUG LABEL
Date: 20240407

ACTIVE INGREDIENTS: MINERAL OIL 3 mg/50 mL; GLYCERIN 2 mg/50 mL
INACTIVE INGREDIENTS: WATER

DOSAGE AND ADMINISTRATION

use as a normal body cream

WARNINGS

For external use only.

INACTIVE INGREDIENT

Aqua

INDICATIONS AND USAGE

Apply to affected area twice per day on cleansed skin.

Keep out of reach of children.

PURPOSE

brighten and restore skin